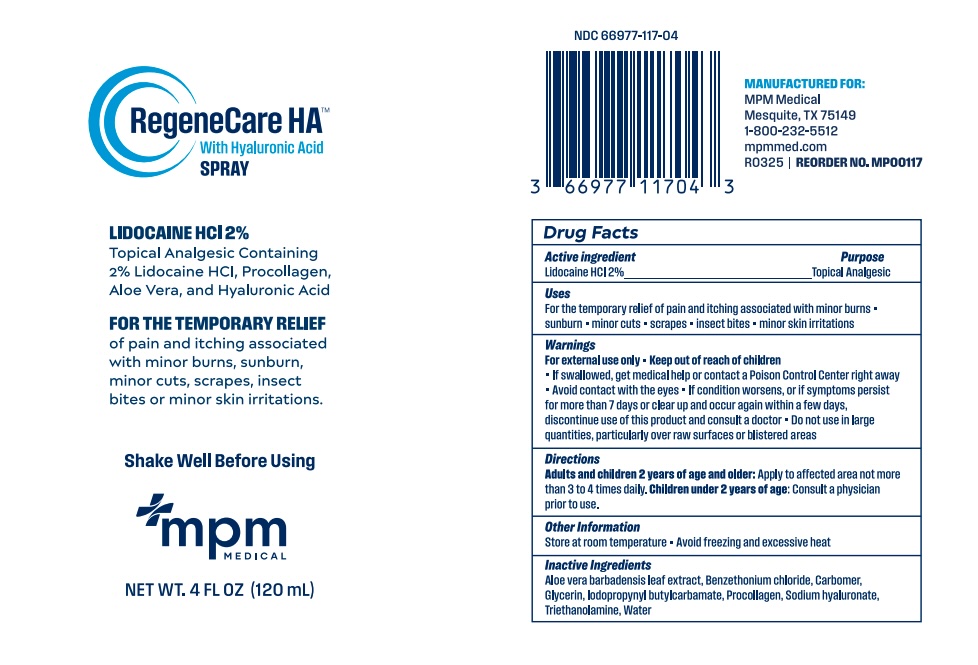 DRUG LABEL: REGENECARE HA
NDC: 66977-117 | Form: GEL
Manufacturer: MPM Medical LLC
Category: otc | Type: HUMAN OTC DRUG LABEL
Date: 20260105

ACTIVE INGREDIENTS: LIDOCAINE HYDROCHLORIDE 20 mg/1 mL
INACTIVE INGREDIENTS: ALOE VERA LEAF; BENZETHONIUM CHLORIDE; CARBOMER 940; GLYCERIN; IODOPROPYNYL BUTYLCARBAMATE; HYALURONATE SODIUM; TROLAMINE; WATER; MARINE COLLAGEN, SOLUBLE

MP00117 MPM Regenecare HA Spray 4 fl.oz.

Active Ingredient

Lidocaine HCl 2%

Purpose

Anesthetic

Uses

For the temporary relief of pain and itching associated with

- minor burns
- sunburn
- minor cuts
- scrapes
- insect bites
- minor skin irritations

Warnings

For external use only

If swallowed, get medical help or contatct a Poison Control Center right away

Avoid contact with the eyes

If condition worsens, or if symptoms persist for more than 7 days or clear up and occur again within a few days, discontinue use of this product and consult with a doctor

Do not use in large quantities, particularly over raw surfaces or blistered areas

Keep out of reach of children

Directions

Adults and children 2 years of age and older: Apply to affected area not more than 3 to 4 times daily.

Children under 2 years of age: Consult a physician prior to use.

Other information

Store at room temperature.

Avoid freezing and excessive heat.

Inactive ingredients

Aloe vera barbadensis leaf extract, Benzethonium chloride, Carbomer, Glycerin, Iodopropynyl butylcarbamate, Procollagen, Sodium hyaluronate, Triethanolamine, Water